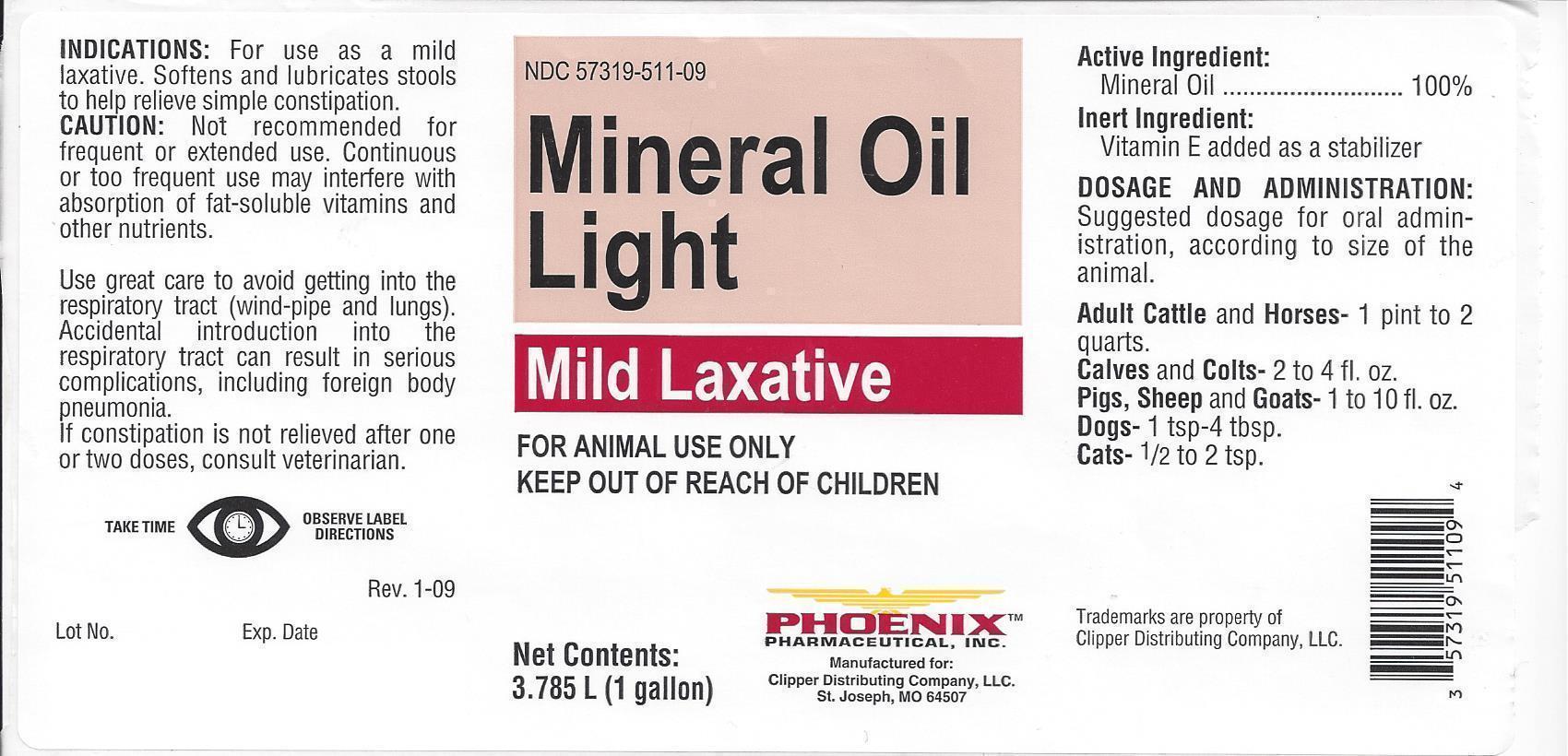 DRUG LABEL: MINERAL OIL LIGHT
NDC: 57319-511 | Form: LIQUID
Manufacturer: Phoenix Pharmaceutical Inc./Clipper Distributing, Inc
Category: animal | Type: OTC ANIMAL DRUG LABEL
Date: 20130903

ACTIVE INGREDIENTS: LIGHT MINERAL OIL 3.45 kg/3.45 kg

PHOENIX MINERAL OIL LIGHT

PACKAGE LABEL

NDC 57319-511-09

Mineral Oil Light

Mild Laxative

FOR ANIMAL USE ONLY

KEEP OUT OF REACH OF CHILDREN

Net Contents:

3.785 L (1 gallon)

PHOENIXTM

PHARMACEUTICAL, INC.

Manufactured for:

Clipper Distributing Company, LLC.

St. Joseph, MO 64507

INDICATIONS:

For use asd a mild laxative. Softens and lubricates stools to help relive simple constipation.

CAUTION:

Not recommended for frequent or extended use. Continuous or too frequent use may interfere with absorption of fat-soluble vitamins and other nutrients.

Use great care to avoid getting into the respiratory tract (wind-pipe and lungs). Accidental introduction into the respiratory tract can result in serious complications, including foreign body pneumonia. If constipation is not relieved after one or two doses, consult veterinarian.

TAKE TIME OBSERVE LABEL DIRECTIONS

Active Ingredient:

Mineral Oil……………………………………….100%

Inert Igredient:

Vitamin E added as a stablizer

DOSAGE AND ADMINISTRATION:

Suggested dosage for oral administration, according to size of animal.

Adult Cattle and Horses– 1 pint to 2 quarts.

Calves and Colts – 2 to 4 fl. oz.

Pigs, Sheep and Goats – 1 to 10 fl. oz.

Dogs- 1 tsp – 4 tbsp.

Cats – ½ to 2 tsp.